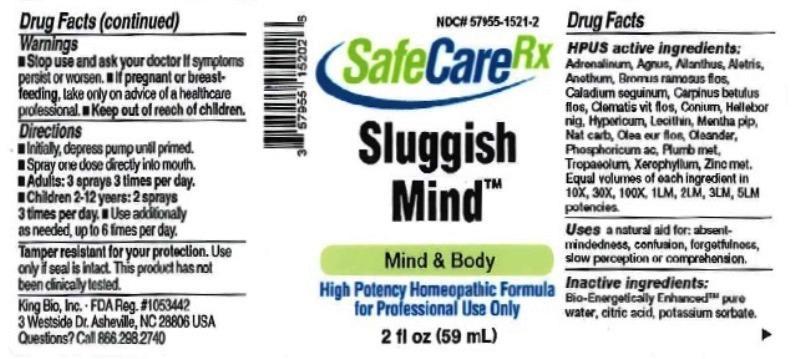 DRUG LABEL: Sluggish Mind
NDC: 57955-1521 | Form: LIQUID
Manufacturer: King Bio Inc.
Category: homeopathic | Type: HUMAN OTC DRUG LABEL
Date: 20161116

ACTIVE INGREDIENTS: EPINEPHRINE 10 [hp_X]/59 mL; CHASTE TREE 10 [hp_X]/59 mL; AILANTHUS ALTISSIMA FLOWERING TWIG 10 [hp_X]/59 mL; ALETRIS FARINOSA ROOT 10 [hp_X]/59 mL; DILL 10 [hp_X]/59 mL; BROMUS RAMOSUS FLOWER 10 [hp_X]/59 mL; DIEFFENBACHIA SEGUINE 10 [hp_X]/59 mL; CARPINUS BETULUS FLOWERING TOP 10 [hp_X]/59 mL; CLEMATIS VITALBA FLOWER 10 [hp_X]/59 mL; CONIUM MACULATUM FLOWERING TOP 10 [hp_X]/59 mL; HELLEBORUS NIGER ROOT 10 [hp_X]/59 mL; HYPERICUM PERFORATUM 10 [hp_X]/59 mL; EGG PHOSPHOLIPIDS 10 [hp_X]/59 mL; MENTHA PIPERITA 10 [hp_X]/59 mL; SODIUM CARBONATE 10 [hp_X]/59 mL; OLEA EUROPAEA FLOWER 10 [hp_X]/59 mL; NERIUM OLEANDER LEAF 10 [hp_X]/59 mL; PHOSPHORIC ACID 10 [hp_X]/59 mL; LEAD 10 [hp_X]/59 mL; TROPAEOLUM MAJUS 10 [hp_X]/59 mL; XEROPHYLLUM ASPHODELOIDES 10 [hp_X]/59 mL; ZINC 10 [hp_X]/59 mL
INACTIVE INGREDIENTS: WATER; ANHYDROUS CITRIC ACID; POTASSIUM SORBATE

Sluggish Mind

ACTIVE INGREDIENT

Drug Facts__________________________________________________________________________________________________________

HPUS active ingredients: Adrenalinum, Agnus castus, Ailanthus glandulosus, Aletris farinosa, Anethum graveolens, Bromus ramosus, flos, Caladium seguinum, Carpinus betulus, flos, Clematis vitalba, flos, Conium maculatum, Helleborus niger, Hypericum perforatum, Lecithin, Mentha piperita, Natrum carbonicum, Olea europaea, flos, Oleander, Phosphoricum acidum, Plumbum metallicum, Tropaeolum majus, Xerophyllum asphodeloides, Zincum metallicum. Equal volumes of each ingredient in 10X, 30X, 100X, 1LM, 2LM, 3LM, 5LM potencies.

INDICATIONS AND USAGE

Uses a natural aid for: absentmindedness, confusion, forgetfulness, slow perception or comprehension.

Inactive Ingredients:

Bio-Energetically Enhanced™ pure water, citric acid and potassium sorbate.

Warnings

- Stop use and ask your doctor if symptoms persist or worsen.
- If pregnant or breast-feeding, take only on advice of a healthcare professional.

- Keep out of reach of children.

Directions

- Initially, depress pump until primed.
- Spray one dose directly into mouth.
- Adults: 3 sprays 3 times per day
- Children 2-12 years: 2 sprays 3 times per day.
- Use additionally as needed, up to 6 times per day.

OTHER SAFETY INFORMATION

Tamper resistant for your protection. Use only if safety seal is intact. This product has not been clinically tested.

PURPOSE

Uses a natural aid for:

- absentmindedness
- confusion
- forgetfulness
- slow perception or comprehension